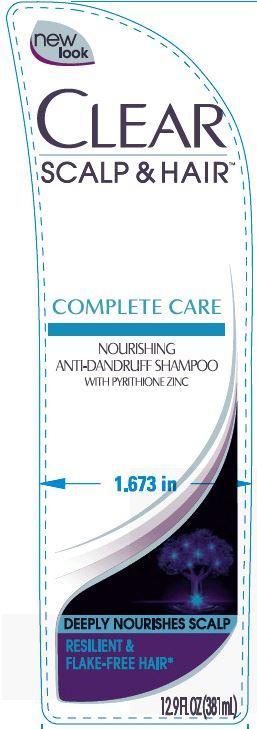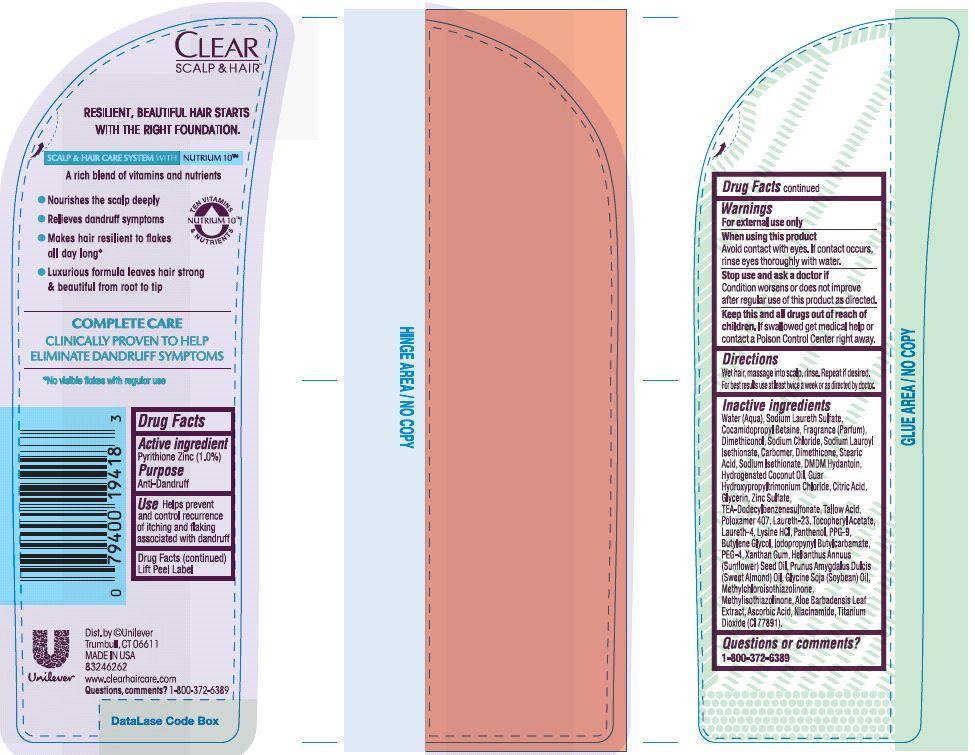 DRUG LABEL: Clear
NDC: 64942-1356 | Form: SHAMPOO
Manufacturer: Conopco Inc. d/b/a Unilever
Category: otc | Type: HUMAN OTC DRUG LABEL
Date: 20140409

ACTIVE INGREDIENTS: Pyrithione Zinc 1.0 g/100 mL
INACTIVE INGREDIENTS: WATER; SODIUM LAURETH SULFATE; COCAMIDOPROPYL BETAINE; SODIUM CHLORIDE; TITANIUM DIOXIDE; SODIUM LAUROYL ISETHIONATE; DMDM HYDANTOIN; TRIETHANOLAMINE DODECYLBENZENESULFONATE; SUNFLOWER OIL; CITRIC ACID MONOHYDRATE; PPG-9; METHYLCHLOROISOTHIAZOLINONE; METHYLISOTHIAZOLINONE; NIACINAMIDE; GUAR HYDROXYPROPYLTRIMONIUM CHLORIDE (1.7 SUBSTITUENTS PER SACCHARIDE); STEARIC ACID; ZINC SULFATE; DIMETHICONOL (41 MPA.S); DIMETHICONE; SODIUM ISETHIONATE; POLOXAMER 407; LAURETH-23; LAURETH-4; .ALPHA.-TOCOPHEROL ACETATE, D-; POLYETHYLENE GLYCOL 400000; PANTHENOL; LYSINE HYDROCHLORIDE; HYDROGENATED COCONUT OIL; SOYBEAN OIL; XANTHAN GUM; ALOE VERA LEAF; ASCORBIC ACID; ALMOND OIL; TALLOW ACID, BEEF; BUTYLENE GLYCOL; IODOPROPYNYL BUTYLCARBAMATE; GLYCERIN

Clear Complete Care Nourishing Anti Dandruff Shampoo PDP and drug facts box

Active Ingredient

Pyrithione Zinc (1.0%)

PURPOSE

PurposeAntidandruff

INDICATIONS AND USAGE

Use Helps prevent and control recurrence of itching and flaking associated with dandruff

Warnings
For external use only

When using this product

Avoid contact with eyes. If contact occurs, rinse eyes thoroughly with water.

Stop use and ask a doctor if

Condition worsens or does not improve after regular use of this product as directed.

KEEP OUT OF REACH OF CHILDREN

Keep this and all drugs out of reach of children. If swallowed, get medical help or contact a Poison Control Center right away.

Directions

Wet hair, massage into scalp, rinse. Repeat if desired. For best results use at least twice a week or as directed by a doctor.

INACTIVE INGREDIENT

Inactive IngredientsWater (Aqua), Sodium Laureth Sulfate, Cocamidopropyl Betaine, Fragrance (Parfum), Dimethiconol, Sodium Chloride, Sodium Lauroyl Isethionate, Carbomer, Dimethicone, Stearic Acid, Sodium Isethionate, DMDM Hydantoin, Hydrogenated Coconut Oil, Guar Hydroxypropyltrimonium Chloride, Citric Acid, Glycerin, Zinc Sulfate, TEA-Dodecylbenzenesulfonate, Tallow Acid, Poloxamer 407, Laureth-23, Tocopheryl Acetate, Laureth-4, Lysine HCl, Panthenol, PPG-9, Butylene Glycol, Iodopropynyl Butylcarbamate, PEG-4, Xanthan Gum, Helianthus Annuus (Sunflower) Seed Oil, Prunus Amygdalus Dulcis (Sweet Almond) Oil, Glycine Soja (Soybean) Oil, Methylchloroisothiazolinone, Methylisothiazolinone, Aloe Barbadensis Leaf Extract, Ascorbic Acid, Niacinamide, Titanium Dioxide (CI 77891)

Questions or comments?

1-800-372-6389